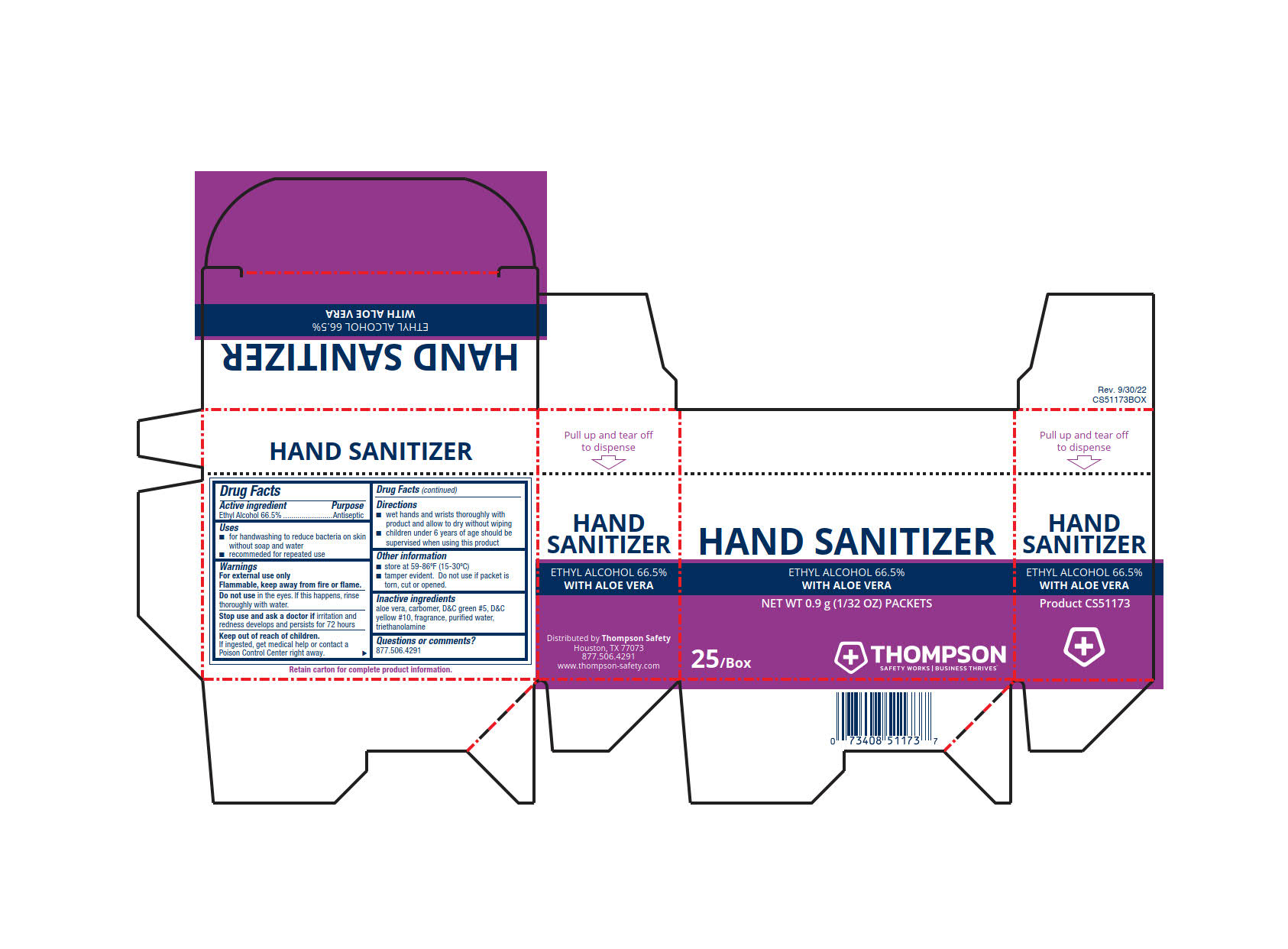 DRUG LABEL: Thompson Hand Sanitizer
NDC: 73408-513 | Form: GEL
Manufacturer: Thompson
Category: otc | Type: HUMAN OTC DRUG LABEL
Date: 20250908

ACTIVE INGREDIENTS: ALCOHOL 540.26 g/1 L
INACTIVE INGREDIENTS: WATER; ALOE; D&C YELLOW NO. 10; CARBOMER INTERPOLYMER TYPE A (ALLYL SUCROSE CROSSLINKED); D&C GREEN NO. 5; TROLAMINE

Thompson Hand Sanitizer

ACTIVE INGREDIENT

Ethyl Alcohol 66.5%

PURPOSE

Antiseptic

INDICATIONS AND USAGE

- for handwashing to reduce bacteria on skin without soap and water
- recommended for repeated use

WARNINGS

For external use only

Flammable, keep away from fire or flame.

Do not use in the eyes. If this happens, rinse thoroughly with water.

Stop use and ask a doctor if irritation and redness develops and persists for 72 hours

KEEP OUT OF REACH OF CHILDREN

If ingested, get medical help or contact a Poison Control Center right away.

DOSAGE AND ADMINISTRATION

- wet hands and wrists thoroughly with product and allow to dry without wiping
- children under 6 years of age should be supervised when using this product

OTHER SAFETY INFORMATION

- store at 59-86°F (15-30°C)
- tamper evident. Do not use if packet is torn, cut or opened.

INACTIVE INGREDIENT

aloe vera. carbomer D&C green #5, D&C yellow #10, fragrance, purified water, triethanolamine

QUESTIONS

877.506.4291

PACKAGE LABEL

HAND SANITIZER

ETHYL ALCOHOL 66.5%

WITH ALOE VERA

NET WT 0.9 G (1/32 OZ) PACKETS

25 /BOX THOMPSON

SAFETY WORKS ǀ BUSINESS THRIVES ᵀᴹ